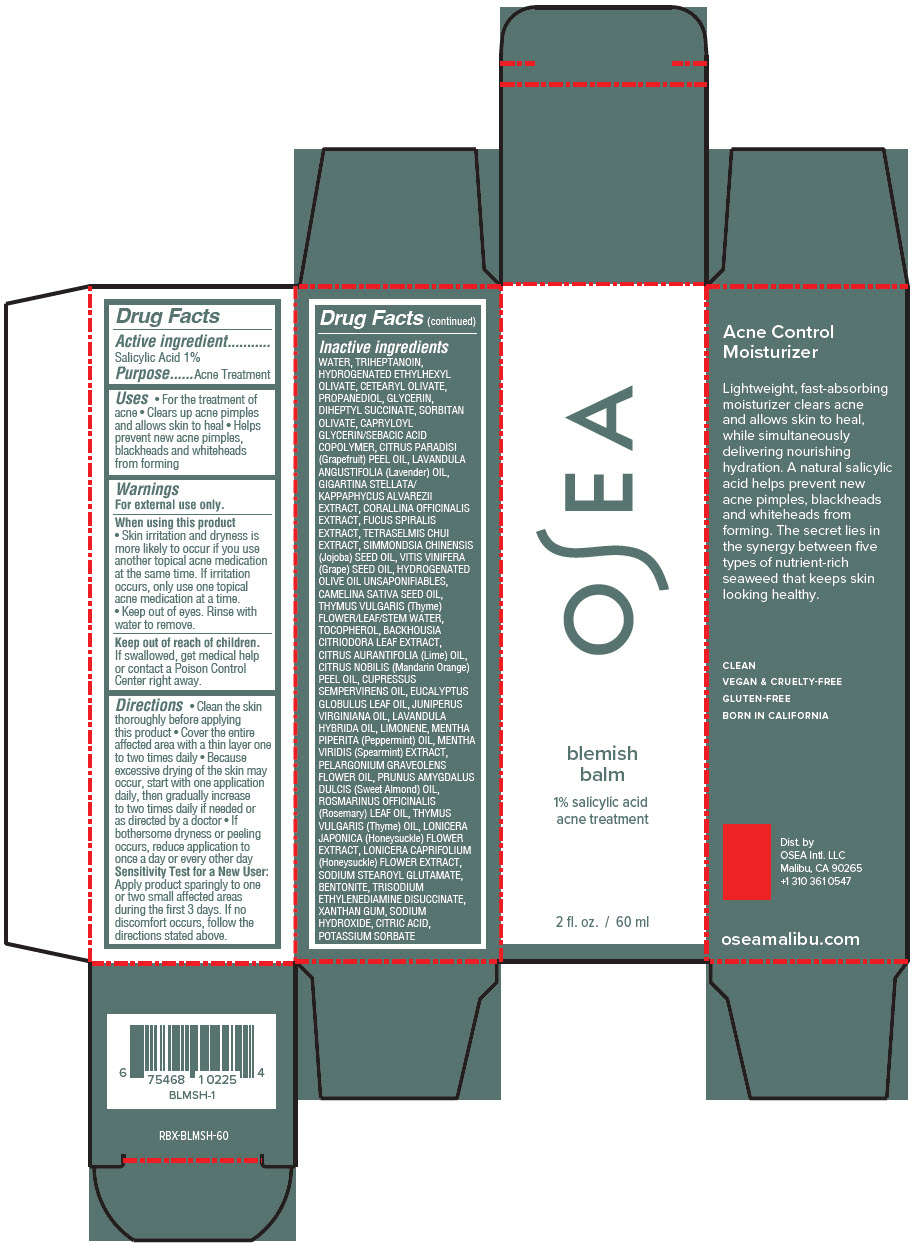 DRUG LABEL: OSEA Blemish Balm
NDC: 73432-002 | Form: CREAM
Manufacturer: OSEA International, LLC
Category: otc | Type: HUMAN OTC DRUG LABEL
Date: 20250129

ACTIVE INGREDIENTS: Salicylic Acid 1 mg/100 mL
INACTIVE INGREDIENTS: water; Triheptanoin; CETEARYL OLIVATE; PROPANEDIOL; GLYCERIN; DIHEPTYL SUCCINATE; SORBITAN OLIVATE; CAPRYLOYL GLYCERIN/SEBACIC ACID COPOLYMER (2000 MPA.S); GRAPEFRUIT OIL; LAVENDER OIL; Mastocarpus stellatus; Kappaphycus alvarezii; CORALLINA OFFICINALIS; FUCUS SPIRALIS; TETRASELMIS CHUI; JOJOBA OIL; GRAPE SEED OIL; HYDROGENATED OLIVE OIL UNSAPONIFIABLES; CAMELINA SATIVA SEED OIL; THYME; TOCOPHEROL; BACKHOUSIA CITRIODORA LEAF; LIME OIL, COLD PRESSED; MANDARIN OIL; CUPRESSUS SEMPERVIRENS LEAF OIL; EUCALYPTUS OIL; JUNIPERUS VIRGINIANA OIL; LAVANDIN OIL; LIMONENE, (+)-; PEPPERMINT OIL; SPEARMINT; PELARGONIUM GRAVEOLENS FLOWER OIL; ALMOND OIL; ROSEMARY OIL; THYME OIL; LONICERA JAPONICA FLOWER; LONICERA CAPRIFOLIUM FLOWER; SODIUM STEAROYL GLUTAMATE; BENTONITE; TRISODIUM ETHYLENEDIAMINE DISUCCINATE; XANTHAN GUM; SODIUM HYDROXIDE; CITRIC ACID MONOHYDRATE; POTASSIUM SORBATE

OSEA Blemish Balm

Drug Facts

Active ingredient

Salicylic Acid 1%

Purpose

Acne Treatment

Uses

- For the treatment of acne
- Clears up acne pimples and allows skin to heal
- Helps prevent new acne pimples, blackheads and whiteheads from forming

Warnings

For external use only.

When using this product

- Skin irritation and dryness is more likely to occur if you use another topical acne medication at the same time. If irritation occurs, only use one topical acne medication at a time.
- Keep out of eyes. Rinse with water to remove.

Keep out of reach of children. If swallowed, get medical help or contact a Poison Control Center right away.

Directions

- Clean the skin thoroughly before applying this product
- Cover the entire affected area with a thin layer one to two times daily
- Because excessive drying of the skin may occur, start with one application daily, then gradually increase to two times daily if needed or as directed by a doctor
- If bothersome dryness or peeling occurs, reduce application to once a day or every other day

Sensitivity Test for a New User

Apply product sparingly to one or two small affected areas during the first 3 days. If no discomfort occurs, follow the directions stated above.

Inactive ingredients

WATER, TRIHEPTANOIN, HYDROGENATED ETHYLHEXYL OLIVATE, CETEARYL OLIVATE, PROPANEDIOL, GLYCERIN, DIHEPTYL SUCCINATE, SORBITAN OLIVATE, CAPRYLOYL GLYCERIN/SEBACIC ACID COPOLYMER, CITRUS PARADISI (Grapefruit) PEEL OIL, LAVANDULA ANGUSTIFOLIA (Lavender) OIL, GIGARTINA STELLATA/ KAPPAPHYCUS ALVAREZII EXTRACT, CORALLINA OFFICINALIS EXTRACT, FUCUS SPIRALIS EXTRACT, TETRASELMIS CHUI EXTRACT, SIMMONDSIA CHINENSIS (Jojoba) SEED OIL, VITIS VINIFERA (Grape) SEED OIL, HYDROGENATED OLIVE OIL UNSAPONIFIABLES, CAMELINA SATIVA SEED OIL, THYMUS VULGARIS (Thyme) FLOWER/LEAF/STEM WATER, TOCOPHEROL, BACKHOUSIA CITRIODORA LEAF EXTRACT, CITRUS AURANTIFOLIA (Lime) OIL, CITRUS NOBILIS (Mandarin Orange) PEEL OIL, CUPRESSUS SEMPERVIRENS OIL, EUCALYPTUS GLOBULUS LEAF OIL, JUNIPERUS VIRGINIANA OIL, LAVANDULA HYBRIDA OIL, LIMONENE, MENTHA PIPERITA (Peppermint) OIL, MENTHA VIRIDIS (Spearmint) EXTRACT, PELARGONIUM GRAVEOLENS FLOWER OIL, PRUNUS AMYGDALUS DULCIS (Sweet Almond) OIL, ROSMARINUS OFFICINALIS (Rosemary) LEAF OIL, THYMUS VULGARIS (Thyme) OIL, LONICERA JAPONICA (Honeysuckle) FLOWER EXTRACT, LONICERA CAPRIFOLIUM (Honeysuckle) FLOWER EXTRACT, SODIUM STEAROYL GLUTAMATE, BENTONITE, TRISODIUM ETHYLENEDIAMINE DISUCCINATE, XANTHAN GUM, SODIUM HYDROXIDE, CITRIC ACID, POTASSIUM SORBATE

Dist. by
OSEA Intl. LLC
Malibu, CA 90265

PRINCIPAL DISPLAY PANEL - 60 ml Bottle Carton

OSEA

blemish
balm

1% salicylic acid
acne treatment

2 fl. oz. / 60 ml